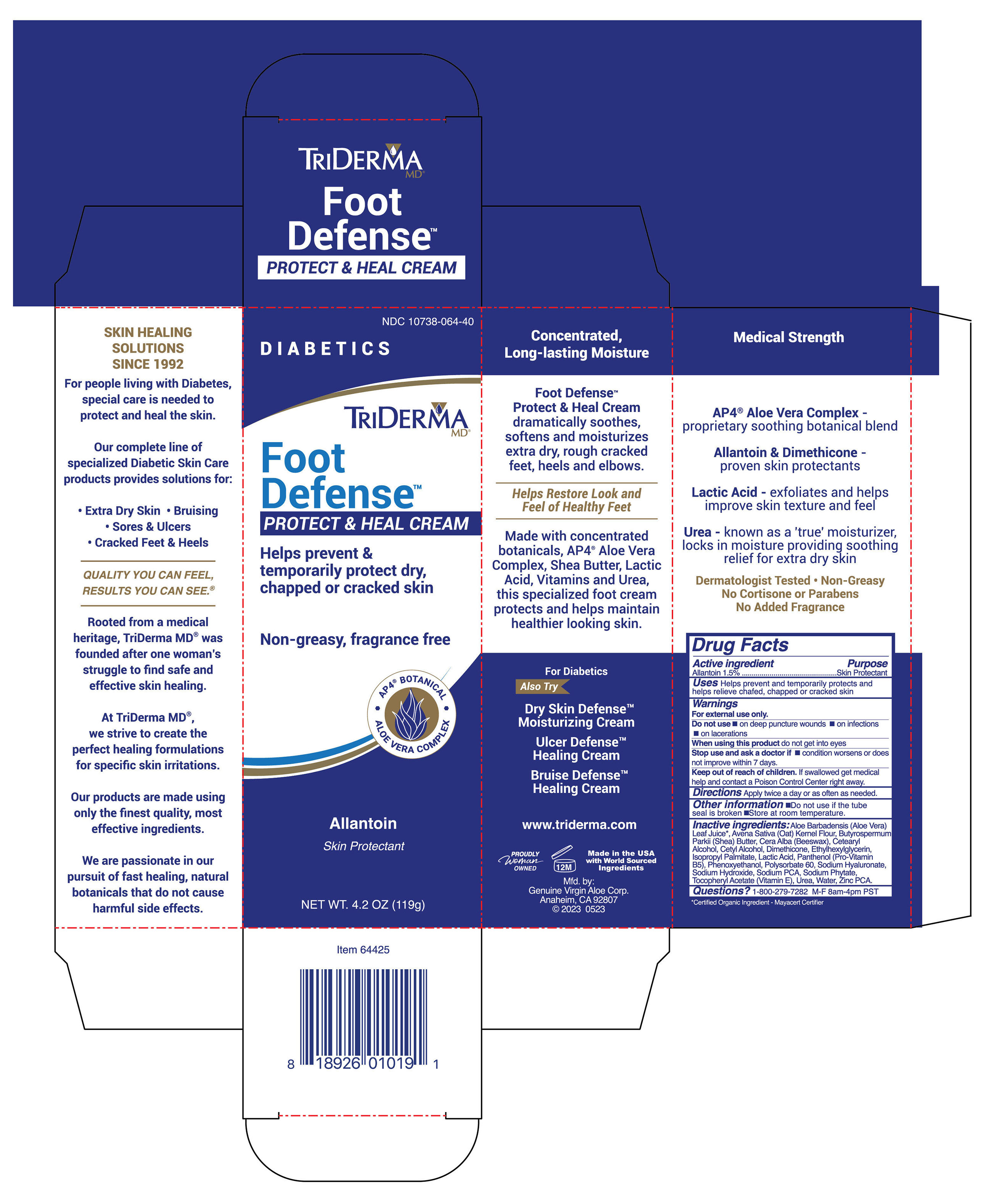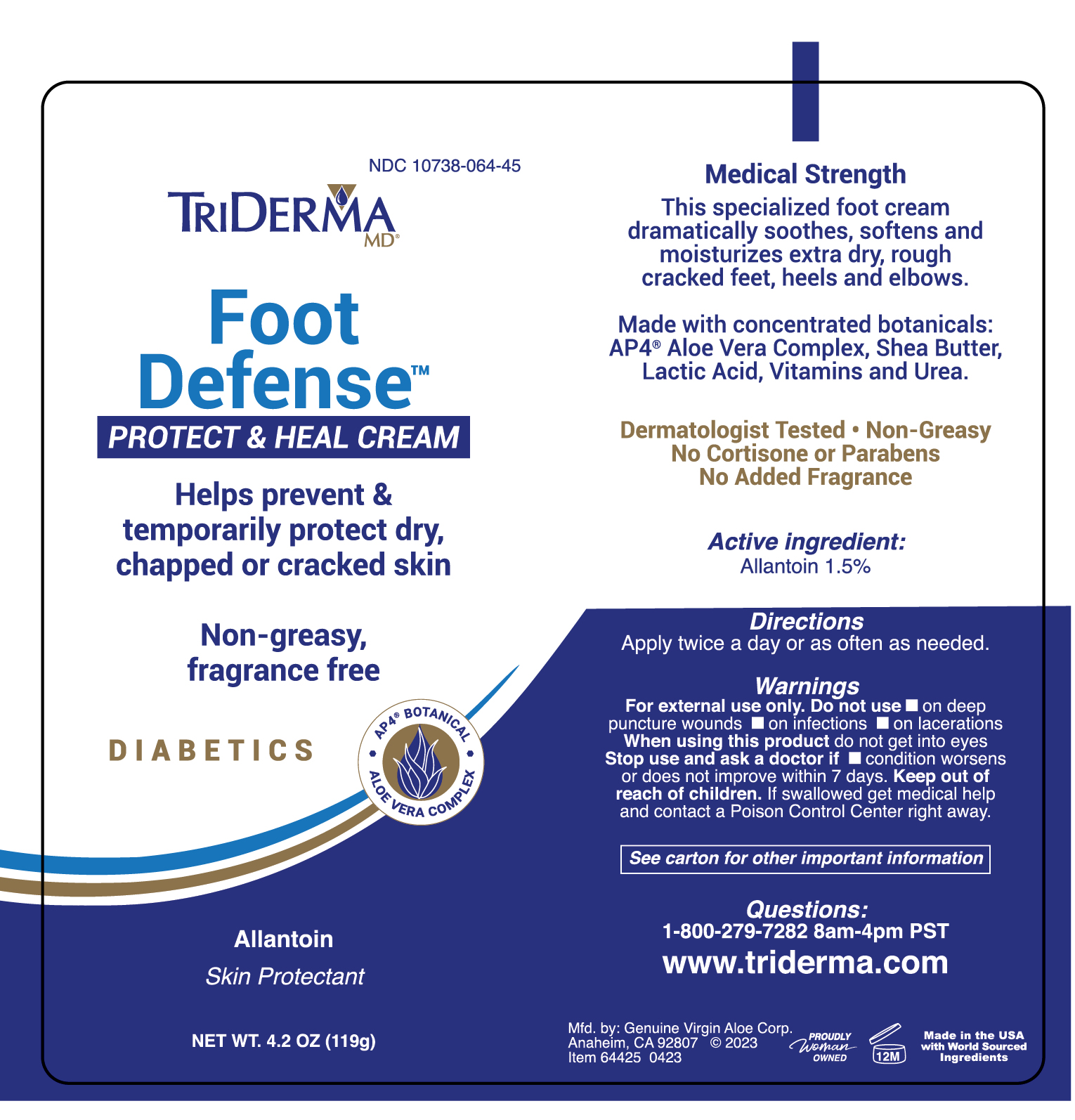 DRUG LABEL: TriDerma Foot Defense
NDC: 10738-064 | Form: CREAM
Manufacturer: Genuine Virgin Aloe Corporation
Category: otc | Type: HUMAN OTC DRUG LABEL
Date: 20260128

ACTIVE INGREDIENTS: ALLANTOIN 15 mg/1 g
INACTIVE INGREDIENTS: ISOPROPYL PALMITATE; ALOE VERA LEAF JUICE; SODIUM HYALURONATE; PANTHENOL; SODIUM PHYTATE; CETYL ALCOHOL; SHEA BUTTER; LACTIC ACID; BEESWAX; SODIUM PCA; ZINC PCA; PHENOXYETHANOL; WATER; .ALPHA.-TOCOPHEROL ACETATE, D-; ETHYLHEXYLGLYCERIN; SODIUM HYDROXIDE; CETEARYL ALCOHOL; DIMETHICONE 100; POLYSORBATE 60; AVENA SATIVA (OAT) STARCH

TriDerma Foot Defense Protect & Heal Cream

ACTIVE INGREDIENT

Allantoin 1.5%

PURPOSE

Skin Protectant

INDICATIONS AND USAGE

Helps prevent and temporarily protects and helps relieve chafed, chapped or cracked skin.

WARNINGS

For external use only.

DO NOT USE

- on deep puncture wounds
- on infections
- on lacerations

WHEN USING

do not get into eyes

stop use and ask a doctor if conditin worsens or does not improve within 7 days.

KEEP OUT OF REACH OF CHILDREN

if swallowed get medical help and contact a poison control center right away.

DOSAGE AND ADMINISTRATION

Apply twice a day or as often as needed.

- Do not use if the tube seal is broken
- Store at room temperatue

QUESTIONS

Questions: 1-800-279-7282 M-F 8 am - 4 pm PST

INACTIVE INGREDIENT

Aloe Barbadensis (Aloe Vera) Leaf Juice*, Avena Sativa (Oat) Kernel Flour, Butyrospermum Parkii (Shea) Butter, Cera Alba (Beeswax), Cetearyl Alcohol, Cetyl Alcohol, Dimethicone, Ethylhexylglycerin, Isopropyl Palmitate, Lactic Acid, Panthenol (Pro-Vitamin B5), Phenoxyethanol, Polysorbate 60, Sodium Hyaluronate, Sodium Hydroxide, Sodium PCA, Sodium Phytate, Tocopheryl Acetate (Vitamin E), Urea, Water, Zinc PCA.

*Certified Organic Ingredient - Mayacert Certifier